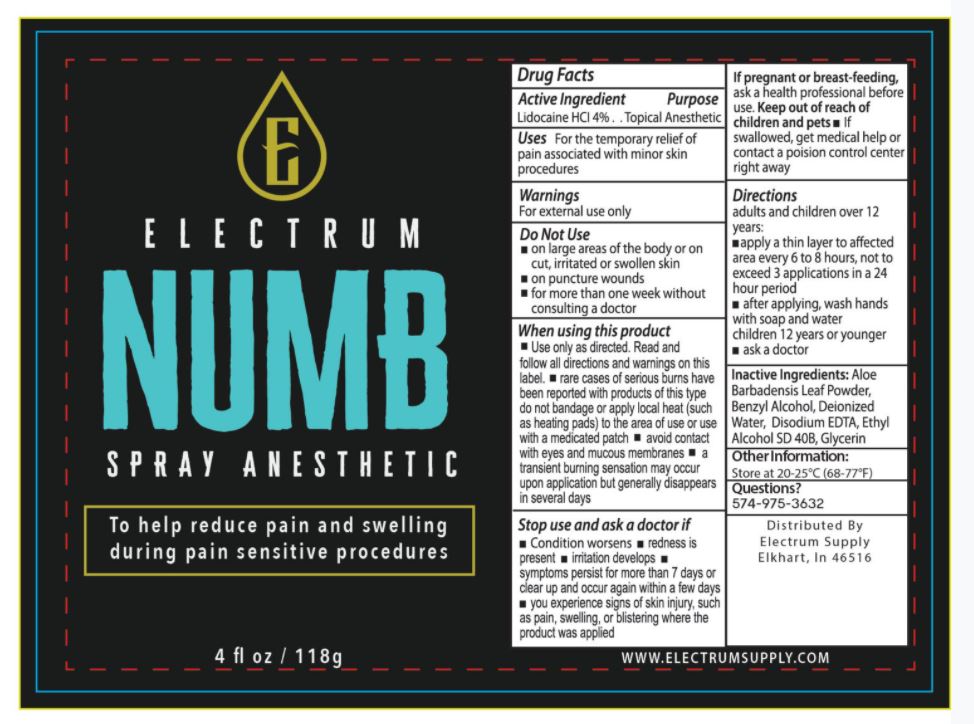 DRUG LABEL: ELECTRUM NUMB ANESTHETIC
NDC: 76348-600 | Form: SPRAY
Manufacturer: RENU LABORATORIES, INC.
Category: otc | Type: HUMAN OTC DRUG LABEL
Date: 20240320

ACTIVE INGREDIENTS: LIDOCAINE HYDROCHLORIDE 4.48 g/112 g
INACTIVE INGREDIENTS: EDETATE DISODIUM; ALCOHOL; ALOE VERA LEAF; BENZYL ALCOHOL; WATER; GLYCERIN

ELECTRUM NUMB SPRAY ANESTHETIC

Active Ingredient

Lidocaine HCl 4%

Purpose

Topical Anesthetic

Uses

For the temporary relief of pain associated with minor skin procedures

Warnings

For external use only

Do Not Use

- on large areas of the body or on cut, irritated or swollen skin
- on puncture wounds
- for more than one week without consulting a doctor

When using this product

- Use only as directed. Read and follow all directions and warnings on this label.
- rare cases of serious burns have been reported with products of this type
- do not bandage or apply local heat (such as heating pads) to the area of use or use with a medicated patch
- avoid contact with eyes and mucous membranes
- a transient burning sensation may occur upon applicator but generally disappears in several days

Stop use and ask a doctor if

- Condition worsens
- redness is present
- irritation develops
- symptoms persist for more than 7 days or clear up and occur again within a few days
- you experience signs of skin injury, such as pain, swelling, or blistering where the product was applied

PREGNANCY OR BREAST FEEDING

If pregnant or breast-feeding, ask a health professional before use.

Keep out of reach of children and pets

- If swallowed, get medical help or contact a poison control center right away

Directions

adults and children over 12 years:

- apply a thin layer to affected area every 6 to 8 hours, not to exceed 3 applications in a 24 hour period
- after applying, wash hands with soap and water
- children 12 years or younger - ask a doctor

INACTIVE INGREDIENT

Inactive Ingredients: Aloe Barbadensis Leaf Powder, Benzyl Alcohol, Deionized Water, Disodium EDTA, Ethyl Alcohol SD 40B, Glycerin

Other Information:

Store at 20-25° C (68 - 77°F)

Questions?

574-975-3632